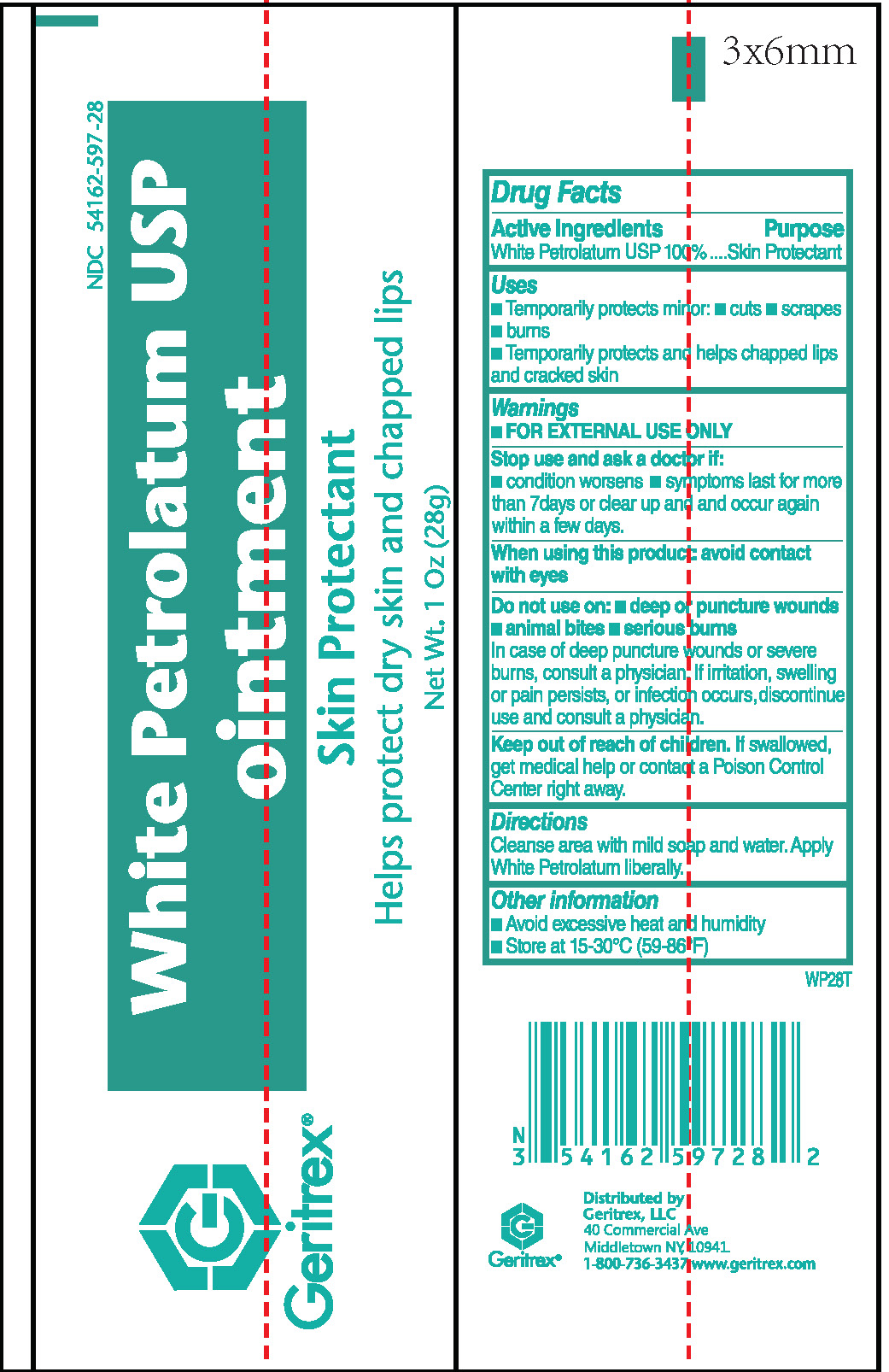 DRUG LABEL: White Petrolatum
NDC: 54162-597 | Form: OINTMENT
Manufacturer: GERITREX LLC
Category: otc | Type: HUMAN OTC DRUG LABEL
Date: 20181012

ACTIVE INGREDIENTS: PETROLATUM 1 g/1 g
INACTIVE INGREDIENTS: ALPHA-TOCOPHEROL 0.001 g/1 g

White Petrolatum USP Ointment

Active Ingredients

White Petrolatum USP 100%

Purpose

Skin Protectant

Uses

- Temporarily protects minor:
- cuts
- scrapes
- burns
- Temporarily protects and helps chapped lips and cracked skin

Warnings

Stop use and ask a doctor if:

- condition worsens
- symptoms last for more than 7 days or clear up and occur again within a few days

Don't not use on:

- deep or puncture wounds
- animal bites
- serious burns

In case of deep puncture wounds or severe burns, consult a physician. If irritation, swelling or pain persists, or infection occurs, discontinue use and consult a physician.

Keep out of reach of children.

If swallowed, get medical help or contact a Poison Control Center right away.

Directions

Cleanse area with mild soap and water. Apply White Petrolatum liberally.

Other information

- Avoid excessive heat and humidity
- Store at 15-30°C (59-86°F)